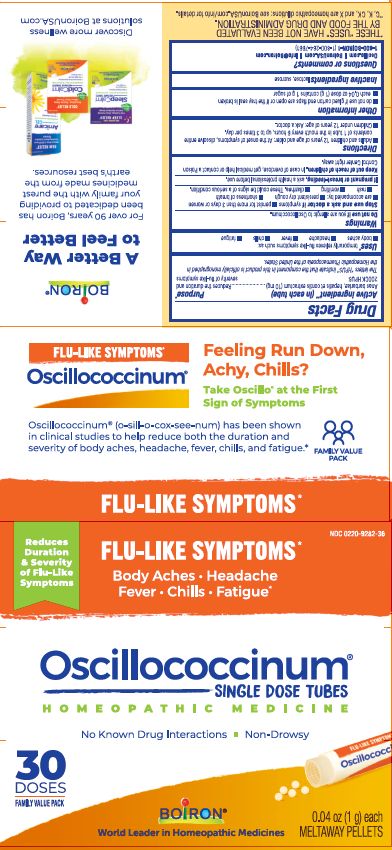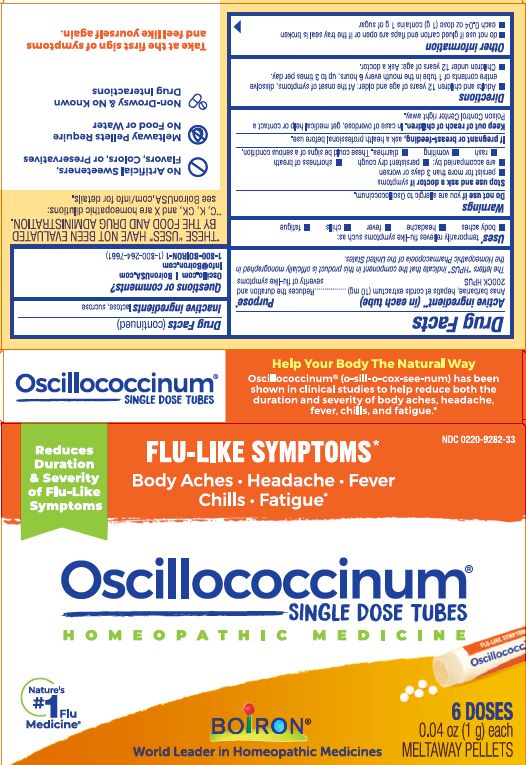 DRUG LABEL: Oscillococcinum
NDC: 0220-9282 | Form: PELLET
Manufacturer: Boiron
Category: homeopathic | Type: HUMAN OTC DRUG LABEL
Date: 20240826

ACTIVE INGREDIENTS: CAIRINA MOSCHATA HEART/LIVER AUTOLYSATE 200 [kp_C]/1 1
INACTIVE INGREDIENTS: SUCROSE; LACTOSE, UNSPECIFIED FORM

Oscillococcinum (CVS +12 yrs)

Active ingredient** (in each tube)

Anas barbariae, hepatis et cordis extractum (10 mg) 200CK HPUS

The letters "HPUS" indicate that the component in this product are officially monographed in the Homeopathic Pharmacopoeia of the United States.

Purpose*

Anas barbariae, hepatis et cordis extractum 200CK (10 mg) HPUS ..... Reduces the duration and severity of flu-like symptoms

Uses*

temporarily relieves flu-like symptoms such as:

- body aches
- headache
- fever
- chills
- fatigue

Do not use if you are allergic to Oscillococcinum.

Stop use and ask a doctor if symptoms

- persist for more than 3 days or worsen
- are accompanied by:
- persistent dry cough
- shortness of breath
- rash
- vomiting
- diarrhea.

These could be signs of a serious condition.

PREGNANCY OR BREAST FEEDING

If pregnant or breast-feeding, ask a health professional before use.

Keep out of reach of children. In case of overdose, get medical help or contact a Poison Control Center right away.

DOSAGE AND ADMINISTRATION

- Adults and children 12 years of age and older: At the onset of symptoms, dissolve entire contents of 1 tube in the mouth every 6 hours, up to 3 times per day.
- Children under 12 years of age: Ask a doctor.

INACTIVE INGREDIENT

lactose, sucrose

QUESTIONS

Oscillo.com
BoironUSA.com
Info@boironusa.com
1-800-BOIRON-1 (1-800-264-7661)
Distributed by Boiron Inc.
Newtown Square, PA 19073

do not use if glued carton end flaps are open or if the tray seal is broken

each 0.04 oz dose (1g) contains 1g of sugar

0.04 oz (1 g) each

Meltaway Pellets

Body Aches, Headache, Fever, Chills, Fatigue*

Flu-like Symptoms*

Non-Drowsy & No Known Drug Interactions

6 Dose

30 Dose

*THESE “USES” HAVE NOT BEEN EVALUATED BY THE FOOD AND DRUG ADMINISTRATION.

*C,K,CK, and X are homeopathic dilutions: see BoironUSA.com/info for details.